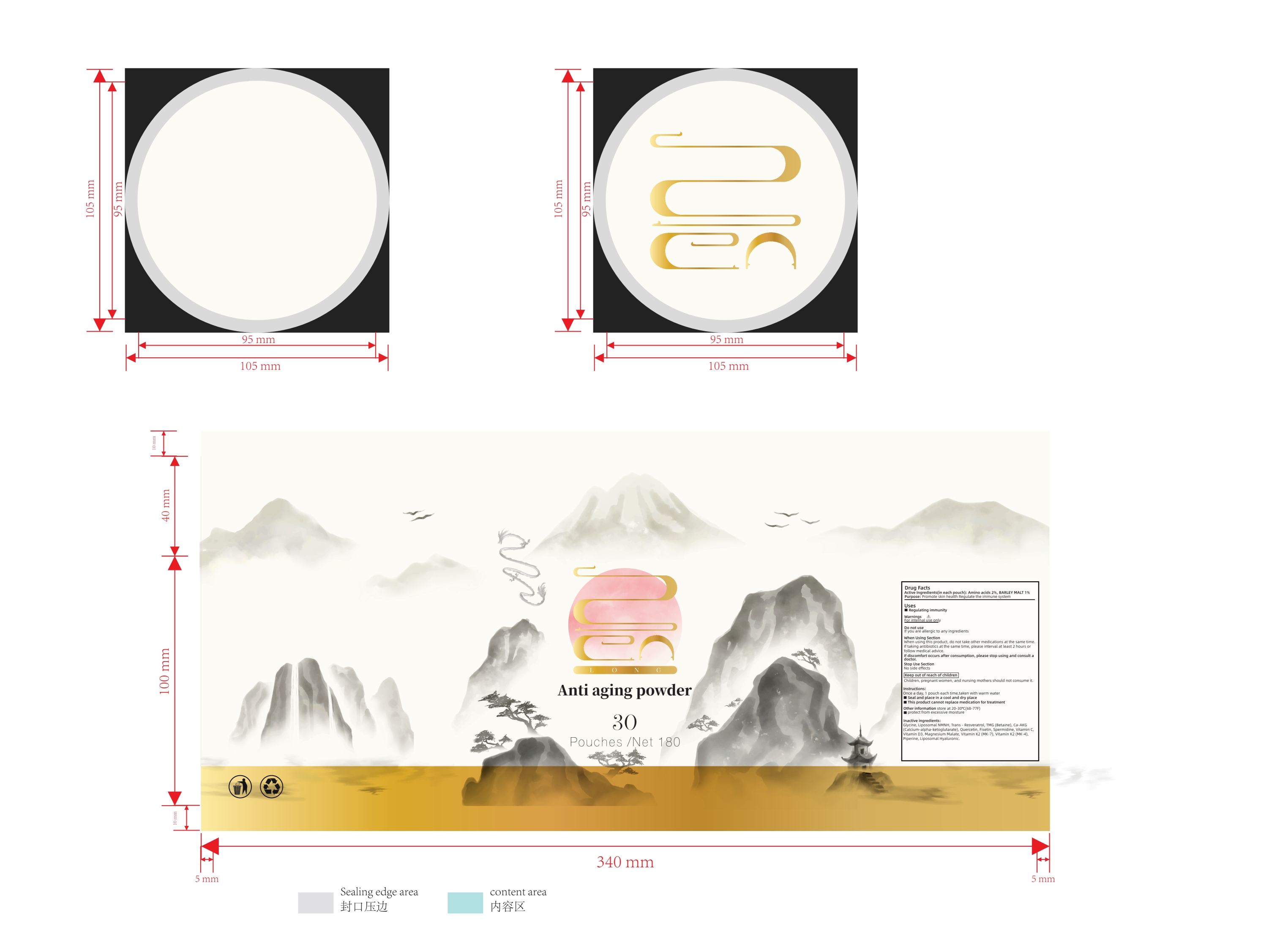 DRUG LABEL: Anti aging
NDC: 83739-002 | Form: POWDER
Manufacturer: XIAN CHIANG COMPANY LIMITED
Category: otc | Type: HUMAN OTC DRUG LABEL
Date: 20250216

ACTIVE INGREDIENTS: AMINO ACIDS 2 g/100 1; BARLEY MALT 1 g/100 1
INACTIVE INGREDIENTS: NICOTINAMIDE MONONUCLEOTIDE; GLYCINE; RESVERATROL; CALCIUM OXOGLURATE; QUERCETIN; FISETIN; CHOLECALCIFEROL; MENAQUINONE 7; ASCORBIC ACID; BETAINE HYDRATE; MENATETRENONE; PIPERINE; SPERMIDINE; MAGNESIUM MALATE; HYALURONIC ACID

83739-002

ACTIVE INGREDIENT

Amino acids 2% BARLEY MALT 1%

Uses

Regulating immunity

Purpose

Promote skin health Regulate the immune system

WARNINGS

For internal use only

Do not use

If you are allergic to any ingredients

When Using Section

When using this product , do not take other medications at the same timeIf taking antibiotics at the same time , please interval at least 2 hours orfollow medical advice.

If discomfort occurs after consumption , please stop using and consult a doctor

Stop Use Section

No side effects

Keep out of reach of childre

Children , pregnant women , and nursing mothers should not consume it .

Instructions

Once a day , 1 pouch each time , taken with warm water

Seal and place in a cool and dry place

This product cannot replace medication for treatment

Other information

Other information store at 20-30°C (68-77F)

protect from excessive moisture

Inactive ingredients

Glycine , Liposomal NMNH , Trans-resveratrol , TMG (Betaine) , CA-AKG(calcium-alpha-ketoglutarate) , Quercetin , Fisetin , Spermidine , Vitamin C ,Vitamin D3 , Magnesium Malate , Vitamin K2 (MK-7) , Vitamin K2 (MK-4)Piperine , Liposomal Hyaluronic